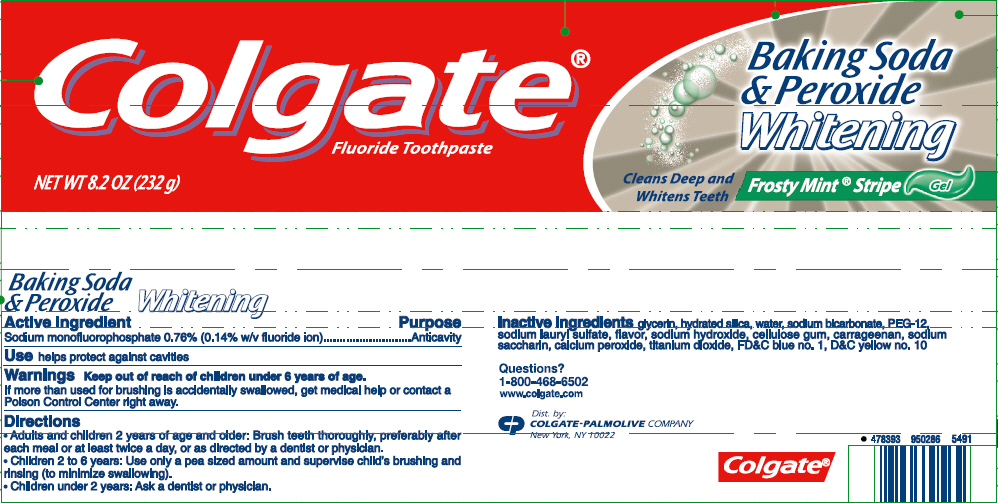 DRUG LABEL: Colgate
NDC: 65954-768 | Form: PASTE, DENTIFRICE
Manufacturer: Mission Hills S.A de C.V
Category: otc | Type: HUMAN OTC DRUG LABEL
Date: 20190429

ACTIVE INGREDIENTS: SODIUM MONOFLUOROPHOSPHATE 1 mg/1 g
INACTIVE INGREDIENTS: GLYCERIN 491.6 mg/1 g; HYDRATED SILICA; WATER; SODIUM BICARBONATE; POLYETHYLENE GLYCOL 600; SODIUM LAURYL SULFATE; SODIUM HYDROXIDE; CARBOXYMETHYLCELLULOSE SODIUM, UNSPECIFIED; CARRAGEENAN; SACCHARIN SODIUM; CALCIUM PEROXIDE; D&C YELLOW NO. 10; FD&C BLUE NO. 1; TITANIUM DIOXIDE

Colgate® Baking Soda and Peroxide Whitening Oxygen Bubbles Frosty Mint® Fluoride Toothpaste

Drug Facts

Active ingredient

Sodium monofluorophosphate 0.76% (0.14% w/v fluoride ion)

Purpose

Anticavity

Use

helps protect against cavities

Warnings

Keep out of reach of children under 6 years of age.

ASK DOCTOR

If more than used for brushing is accidentally swallowed, get medical help or contact a Poison Control Center right away.

Directions

adults and children 2 years of age and older | brush teeth thoroughly, preferably after each meal or at least twice a day, or as directed by a dentist or physician
children 2 to 6 years | use only a pea sized amount and supervise child's brushing and rinsing (to minimize swallowing)
children under 2 years | ask a dentist or physician

Inactive ingredients

glycerin, hydrated silica, water, sodium bicarbonate, PEG-12, sodium lauryl sulfate, flavor, sodium hydroxide, cellulose gum, carrageenan, sodium saccharin, calcium peroxide, titanium dioxide, FD&C blue no. 1, D&C yellow no. 10

Questions?

1-800-468-6502

Dist. by:
COLGATE-PALMOLIVE COMPANY
New York, NY 10022

PRINCIPAL DISPLAY PANEL - 232 g Tube Label

Colgate®
Fluoride Toothpaste

NET WT 8.2 OZ (232 g)

Baking Soda
& Peroxide
Whitening

Cleans Deep and
Whitens Teeth

Frosty Mint® Stripe Gel